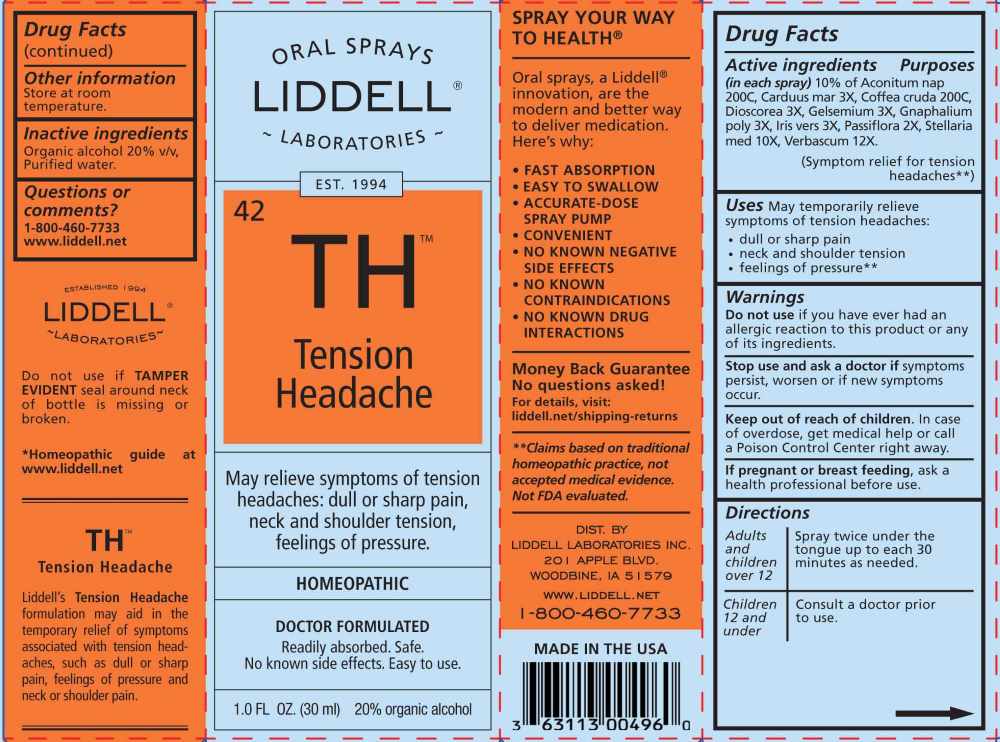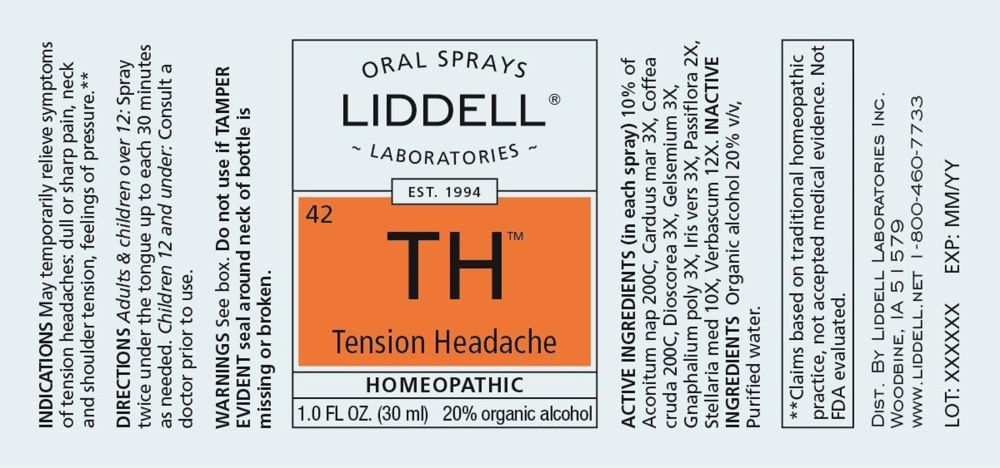 DRUG LABEL: Tension Headache
NDC: 50845-0282 | Form: SPRAY
Manufacturer: Liddell Laboratories, Inc.
Category: homeopathic | Type: HUMAN OTC DRUG LABEL
Date: 20251120

ACTIVE INGREDIENTS: ACONITUM NAPELLUS WHOLE 200 [hp_C]/1 mL; MILK THISTLE 3 [hp_X]/1 mL; ARABICA COFFEE BEAN 200 [hp_C]/1 mL; DIOSCOREA VILLOSA TUBER 3 [hp_X]/1 mL; GELSEMIUM SEMPERVIRENS ROOT 3 [hp_X]/1 mL; PSEUDOGNAPHALIUM OBTUSIFOLIUM WHOLE 3 [hp_X]/1 mL; IRIS VERSICOLOR ROOT 3 [hp_X]/1 mL; PASSIFLORA INCARNATA FLOWERING TOP 2 [hp_X]/1 mL; STELLARIA MEDIA 10 [hp_X]/1 mL; VERBASCUM THAPSUS WHOLE 12 [hp_X]/1 mL
INACTIVE INGREDIENTS: WATER; ALCOHOL

DRUG FACTS:

ACTIVE INGREDIENTS:

(in each spray) 10% of Aconitum Napellus 200C, Carduus Marianus 3X, Coffea Cruda 200C, Dioscorea Villosa 3X, Gelsemium Sempervirens 3X, Gnaphalium Polycephalum 3X, Iris Versicolor 3X, Passiflora Incarnata 2X, Stellaria Media 10X, Verbascum Thapsus 12X.

PURPOSE:

May temporarily relieve symptoms of tension headaches:

• dull or sharp pain

• neck and shoulder tension

• feelings of pressure**

**Claims based on traditional homeopathic practice, not accepted medical evidence. Not FDA evaluated.

WARNINGS:

Do not use if you have ever had an allergic reaction to this product or any of its ingredients.

Stop use and ask a doctor if symptoms persist, worsen or if new symptoms occur.

Keep out of reach of children. In case of overdose, get medical help or call a Poison Control Center right away.

If pregnant or breast feeding, ask a health professional before use.

Do not use if TAMPER EVIDENT seal around neck of bottle is missing or broken.

Store at room temperature.

KEEP OUT OF REACH OF CHILDREN:

In case of overdose, get medical help or call a Poison Control Center right away.

DIRECTIONS:

Adults and children over 12: Spray twice under the tongue up to each 30 minutes as needed.

Children 12 and under: Consult a doctor prior to use.

INDICATIONS:

May temporarily relieve symptoms of tension headaches:

• dull or sharp pain

• neck and shoulder tension

• feelings of pressure**

**Claims based on traditional homeopathic practice, not accepted medical evidence. Not FDA evaluated.

INACTIVE INGREDIENTS:

Organic alcohol 20% v/v, Purified water.

QUESTIONS:

DIST. BY

LIDDELL LABORATORIES, INC.

201 APPLE BLVD.

WOODBINE, IA 51579

WWW.LIDDELL.NET

1-800-460-7733

PACKAGE LABEL DISPLAY:

ORAL SPRAYS

LIDDELL ®

LABORATORIES

EST. 1994

42 TH

Tension Headache

HOMEOPATHIC

1.0 FL OZ (30 ml)